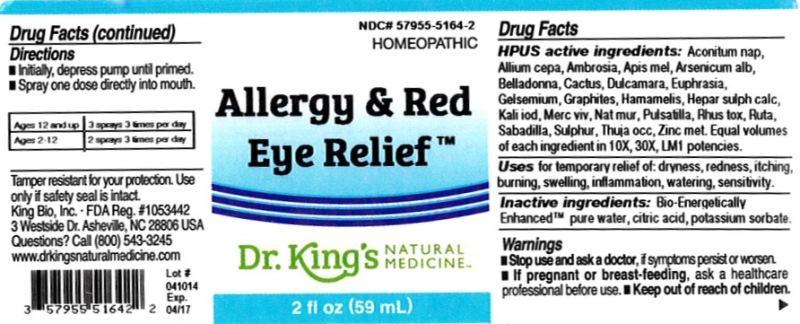 DRUG LABEL: Allergy and Red Eye Relief
NDC: 57955-5164 | Form: LIQUID
Manufacturer: King Bio Inc.
Category: homeopathic | Type: HUMAN OTC DRUG LABEL
Date: 20140422

ACTIVE INGREDIENTS: ACONITUM NAPELLUS 10 [hp_X]/59 mL; ONION 10 [hp_X]/59 mL; AMBROSIA ARTEMISIIFOLIA 10 [hp_X]/59 mL; APIS MELLIFERA 10 [hp_X]/59 mL; ARSENIC TRIOXIDE 10 [hp_X]/59 mL; ATROPA BELLADONNA 10 [hp_X]/59 mL; SELENICEREUS GRANDIFLORUS STEM 10 [hp_X]/59 mL; SOLANUM DULCAMARA TOP 10 [hp_X]/59 mL; EUPHRASIA STRICTA 10 [hp_X]/59 mL; GELSEMIUM SEMPERVIRENS ROOT 10 [hp_X]/59 mL; GRAPHITE 10 [hp_X]/59 mL; HAMAMELIS VIRGINIANA ROOT BARK/STEM BARK 10 [hp_X]/59 mL; CALCIUM SULFIDE 10 [hp_X]/59 mL; POTASSIUM IODIDE 10 [hp_X]/59 mL; MERCURY 10 [hp_X]/59 mL; SODIUM CHLORIDE 10 [hp_X]/59 mL; PULSATILLA VULGARIS 10 [hp_X]/59 mL; TOXICODENDRON PUBESCENS LEAF 10 [hp_X]/59 mL; RUTA GRAVEOLENS FLOWERING TOP 10 [hp_X]/59 mL; SCHOENOCAULON OFFICINALE SEED 10 [hp_X]/59 mL; SULFUR 10 [hp_X]/59 mL; THUJA OCCIDENTALIS LEAFY TWIG 10 [hp_X]/59 mL; ZINC 10 [hp_X]/59 mL
INACTIVE INGREDIENTS: WATER; CITRIC ACID MONOHYDRATE; POTASSIUM SORBATE

Allergy and Red Eye Relief™

ACTIVE INGREDIENT

Drug Facts__________________________________________________________________________________________________________

HPUS activeingredients: Aconitum napellus, Allium cepa, Ambrosia artemisiaefolia, Apis mellifica, Arsenicum album, Belladonna, Cactus grandiflorus, Dulcamara, Euphrasia officinalis, Gelsemium sempervirens, Graphites, Hamamelis virginiana, Hepar sulphuris calcareum, Kali iodatum, Mercurius vivus, Natrum muriaticum, Pulsatilla, Rhus toxicodendron, Ruta graveolens, Sabadilla, Sulphur, Thuja occidentalis, Zincum metallicum. Equal volumes of each ingredient in 10X, 30X, LM1 potencies.

INDICATIONS AND USAGE

Uses for temporary relief of: dryness, redness, itching, burning, swelling, inflammation, watering, sensitivity.

Inactive Ingredients:

Bio-Energetically Enhanced™ pure water, citric acid and potassium sorbate.

Warnings

- Stop use and ask your doctor if symptoms persist or worsen.
- If pregnant or breast-feeding, ask a healthcare professional before use.

- Keep out of reach of children.

Directions

- Initially, depress pump until primed.
- Spray one dose directly into mouth.
- Ages 12 and up: 3 sprays 3 times per day.
- Ages 2-12: 2 sprays 3 times per day

OTHER SAFETY INFORMATION

Tamper resistant for your protection. Use only if safety seal is intact.

PURPOSE

Uses for temporary relief of:

- dryness
- redness
- itching
- burning
- swelling
- inflammation
- watering
- sensitivity